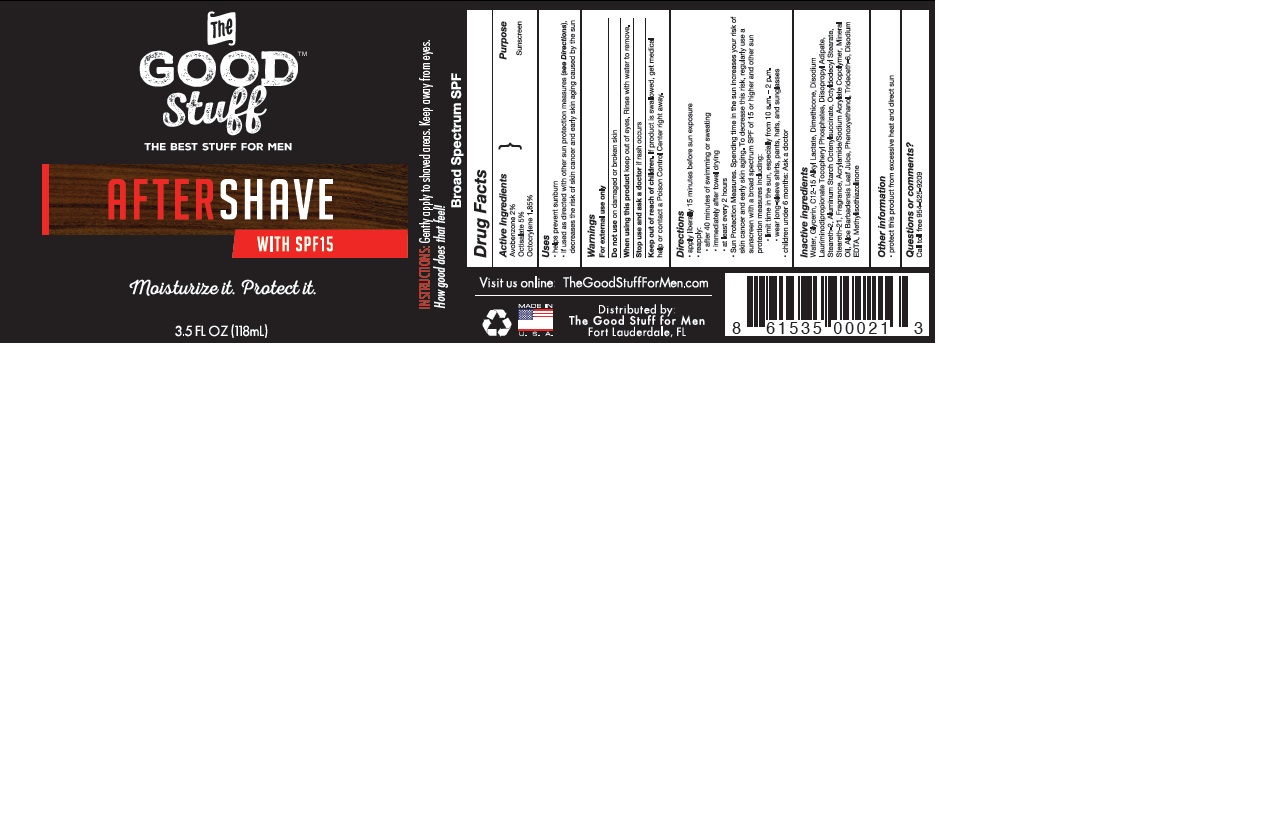 DRUG LABEL: The Good Stuff
NDC: 58443-0198 | Form: CREAM
Manufacturer: Prime Enterprises Inc.
Category: otc | Type: HUMAN OTC DRUG LABEL
Date: 20200117

ACTIVE INGREDIENTS: AVOBENZONE 20 mg/1 mL; OCTOCRYLENE 18.5 mg/1 mL; OCTISALATE 50 mg/1 mL
INACTIVE INGREDIENTS: METHYLISOTHIAZOLINONE; DISODIUM LAURIMINODIPROPIONATE TOCOPHERYL PHOSPHATES; GLYCERIN; MINERAL OIL; STEARETH-2; STEARETH-21; OCTYLDODECYL STEARATE; ALUMINUM STARCH OCTENYLSUCCINATE; DIISOPROPYL ADIPATE; DIMETHICONE; TRIDECETH-6; C12-15 ALKYL LACTATE; PHENOXYETHANOL; WATER; ALOE VERA LEAF; EDETATE DISODIUM; SODIUM ACRYLOYLDIMETHYLTAURATE-ACRYLAMIDE COPOLYMER (1:1; 90000-150000 MPA.S)

The Good Stuff After Shave SPF 15

Active Ingredients

Avobenzone 2%

Octisalate 5%

Octocrylene 1.85%

Purpose

Sunscreen

Uses

- helps prevent sunburn
- if used as directed with other sun protection measures (see Directions), decreases the risk of skin cancer and early skin aging caused by the sun

Warnings

For external use only

Do not use on damaged or broken skin

When using this product keep out of eyes.

Rinse with water to remove.

Stop use and ask a doctor if rash occurs.

Keep out of reach of children. If product is swallowed, get medical help or contact a Poison Control Center right away.

Directions

- apply liberally 15 minutes before sun exposure
- reapply:
- after 40 minutes of swimming or sweating
- immediately after towel drying
- at least every 2 hours
- Sun protection measures . Spending time in the sun increases your risk of skin cancer and early skin aging. To decrease this risk, regularly use a sunscreen spectrum SPF of 15 or higher and other sun protection measures including:
- limit time in the sun, especially from 10 a.m. - 2 p.m
- wear long-sleeved shirts, pants, hats, and sunglasses
- children under 6 months: Ask a doctor

Inactive Ingredients

Water, Glycerin, C12-15 Alkyl Lactate, Dimethicone, Disodium Lauriminodipropionate Tocopheryl Phosphates, Diisopropyl Adipate, Steareth-2, Aluminum Starch Octenylsuccinate, Octyldodecyl Stearate, Steareth-21, Fragrance, Acrylamide/Sodium Acrylate Copolymer, Mineral Oil, Aloe Barbadensis Leaf Juice, Phenoxyethanol, Trideceth-6, Disodium EDTA, Methylisothiazolinone

Other Information

- protect this product from excessive heat and direct sun

Questions or comments?

- Call toll free 954-525-9209